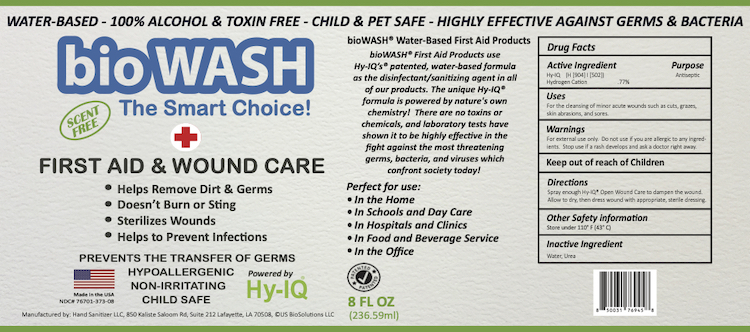 DRUG LABEL: BioWash
NDC: 76701-376 | Form: SPRAY
Manufacturer: Hand Sanitizer LLC
Category: otc | Type: HUMAN OTC DRUG LABEL
Date: 20210814

ACTIVE INGREDIENTS: HYDROGEN CATION 10 mg/1 mL
INACTIVE INGREDIENTS: WATER 940 mg/1 mL; UREA 50 mg/1 mL

Active Ingredient

Hy-IQ (H904) (H502)

Hydrogen Cation .77%

Purpose

Antiseptic

Uses

For the cleaning of minor acute wounds wuch as cuts, grazes, skin abrasions, and sores.

Warnings

For external use only. Do not use if you are allergic to any ingredients. Stop use if rash develops and ask a doctor right away.

Keep Out of Reach of Children

Directions

Spray enough Hy-IQ Open Wound Care to dampen the wound. Allow to dry, then dress wound with appropriate, sterile dressing.

Other Safety Information

Store under 110º F (43º C)

Inactive Ingredient

Water, Urea